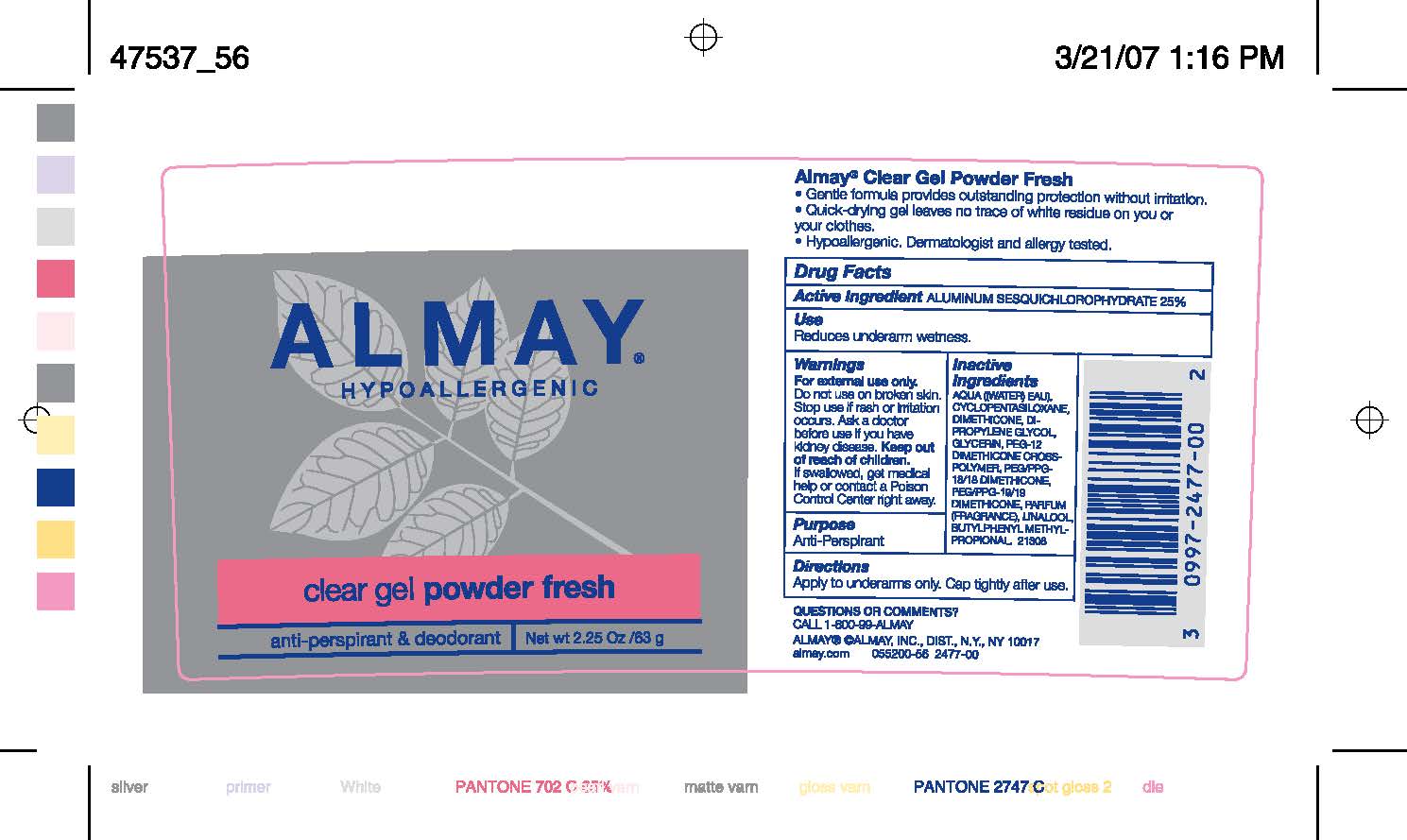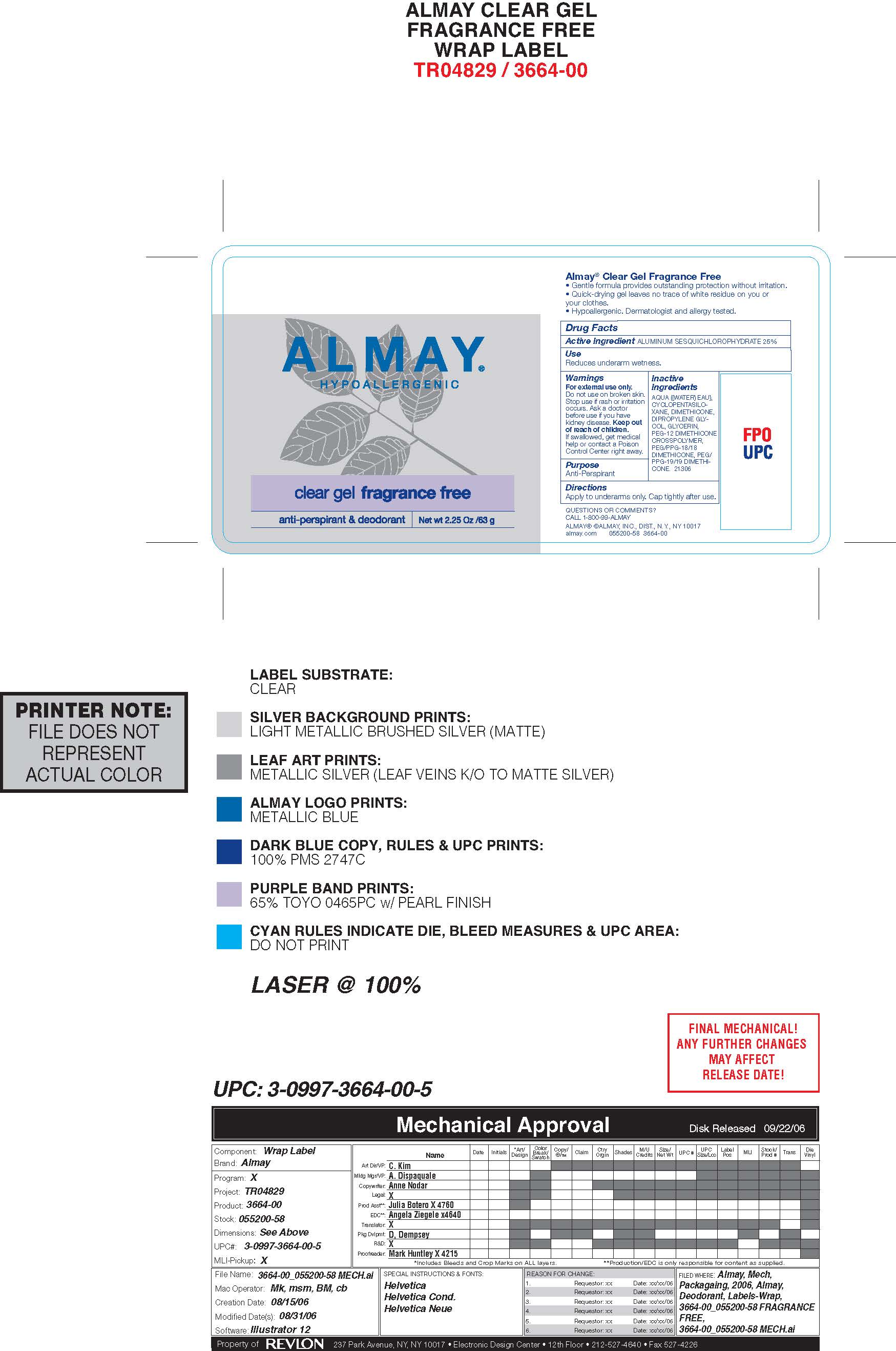 DRUG LABEL: Almay Antiperspirant Clear Gel
NDC: 0311-0736 | Form: GEL
Manufacturer: Almay, Inc.
Category: otc | Type: HUMAN OTC DRUG LABEL
Date: 20241231

ACTIVE INGREDIENTS: ALUMINUM SESQUICHLOROHYDRATE 0.25 g/1 mL
INACTIVE INGREDIENTS: WATER; CYCLOPENTASILOXANE; DIMETHICONE; GLYCERIN; DIPROPYLENE GLYCOL; PEG-12 DIMETHICONE; PEG/PPG-19/19 DIMETHICONE; PEG/PPG-18/18 DIMETHICONE

Almay Anitperspirant Clear Gel - Fragrance Free

ACTIVE INGREDIENT

Aluminum Sesquicholorhydrate 25%

Purpose

Antiperspirant

Warnings:

For external use only.

Do not use on broken skin

Ask a doctor before use if you have kidney disease

Stop use if rash or irriation occurs

KEEP OUT OF REACH OF CHILDREN

If swallowed, get medical help or contact a Poison Control Center right away.

Inactive Ingredients

AQUA ((WATER) EAU), CYCLOPENTASILOXANE, DIMETHICONE, DIPROPYLENE GLYCOL, GLYCERIN, PEG-12 DIMETHICONE CROSSPOLYMER, PEG/PPG-18/18 DIMETHICONE, PEG/PPG-19/19 DIMETHICONE, LINALOOL, BUTYLPHENYL METHYLPROPIONAL

INDICATIONS AND USAGE

Reduces underarm wetness

PACKAGE LABEL

Almay Clear Gel

Powder Fresh

Net Wt. 2.25oz/65g

PACKAGE LABEL

Almay Clear Gel Unscented

Net Wt. 2.25oz/65g